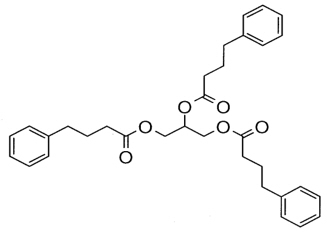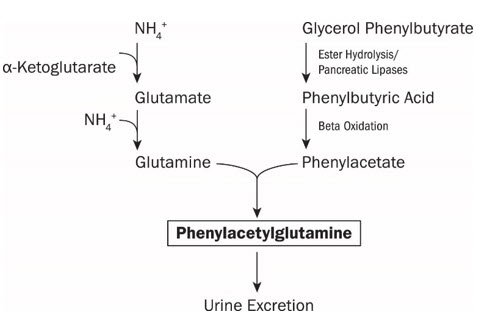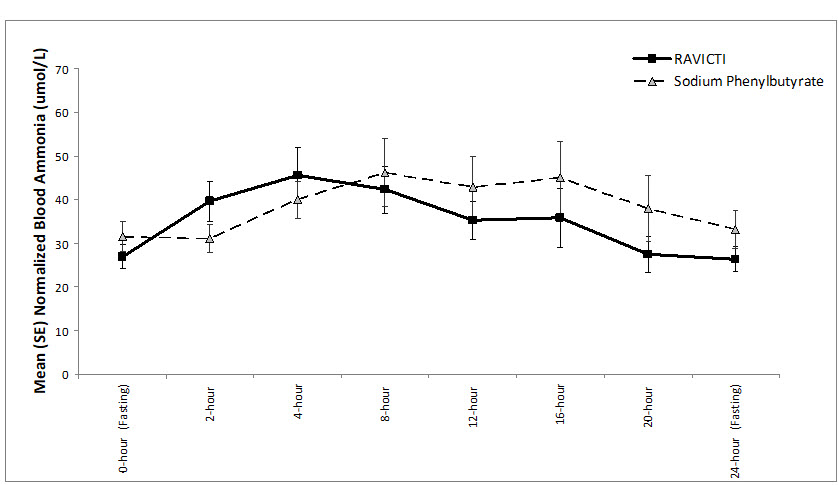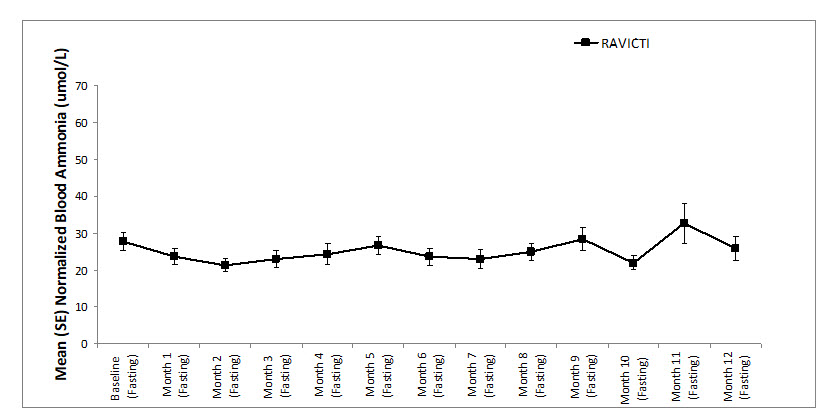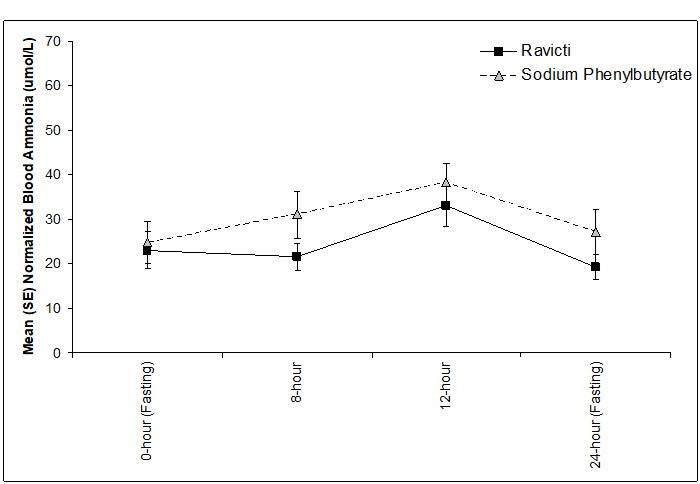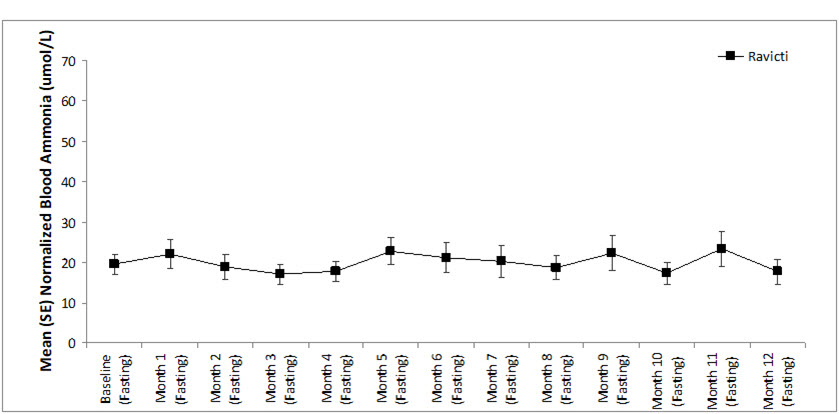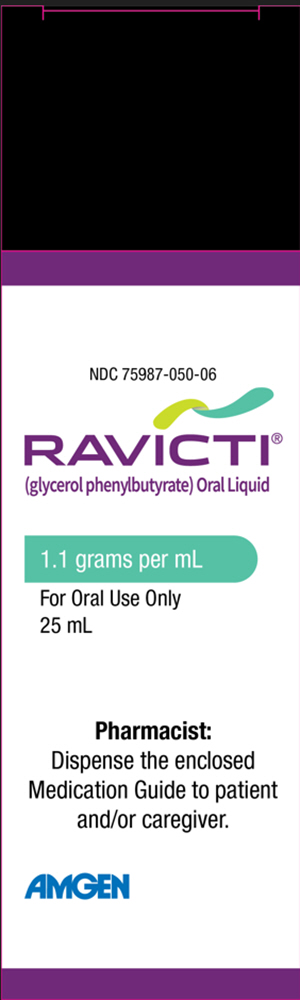 DRUG LABEL: Ravicti
NDC: 75987-050 | Form: LIQUID
Manufacturer: Horizon Therapeutics USA, Inc.
Category: prescription | Type: HUMAN PRESCRIPTION DRUG LABEL
Date: 20251029

ACTIVE INGREDIENTS: GLYCEROL PHENYLBUTYRATE 1.1 g/1 mL

HIGHLIGHTS OF PRESCRIBING INFORMATION

These highlights do not include all the information needed to use RAVICTI safely and effectively. See full prescribing information for RAVICTI.
RAVICTI® (glycerol phenylbutyrate) oral liquid
Initial U.S. Approval: 1996

1 INDICATIONS AND USAGE

RAVICTI is a nitrogen-binding agent indicated for chronic management of patients with urea cycle disorders (UCDs) who cannot be managed by dietary protein restriction and/or amino acid supplementation alone. RAVICTI must be used with dietary protein restriction and, in some cases, dietary supplements. (1)

Limitations of Use:

- RAVICTI is not indicated for treatment of acute hyperammonemia in patients with UCDs. (1)
- Safety and efficacy for treatment of N-acetylglutamate synthase (NAGS) deficiency has not been established. (1)

2 DOSAGE AND ADMINISTRATION

- RAVICTI should be prescribed by a physician experienced in management of UCDs. For administration and preparation, see full prescribing information. (2.1, 2.6)

Switching From Sodium Phenylbutyrate Tablets or Powder to RAVICTI:

- Patients should receive the dosage of RAVICTI that contains the same amount of phenylbutyric acid, see full prescribing information for conversion. (2.2)

Initial Dosage in Phenylbutyrate-Naïve Patients (2.3):

- Recommended dosage range is 4.5 to 11.2 mL/m^2/day (5 to 12.4 g/m^2/day).
- For patients with some residual enzyme activity not adequately controlled with dietary restriction, the recommended starting dose is 4.5 mL/m^2/day.
- Take into account patient's estimated urea synthetic capacity, dietary protein intake, and diet adherence.

Dosage Adjustment and Monitoring:

- Follow plasma ammonia levels to determine the need for dosage titration. (2.4)

Dosage Modifications in Patients with Hepatic Impairment:

- Start dosage at lower end of range. (2.5, 8.7)

3 DOSAGE FORMS AND STRENGTHS

Oral liquid: 1.1 g/mL. (3)

4 CONTRAINDICATIONS

Known hypersensitivity to phenylbutyrate. (4)

5 WARNINGS AND PRECAUTIONS

- Neurotoxicity: Phenylacetate (PAA), the active moiety of RAVICTI, may be toxic; reduce dosage for symptoms of neurotoxicity. (5.1)
- Pancreatic Insufficiency or Intestinal Malabsorption: Monitor ammonia levels closely. (5.2)

6 ADVERSE REACTIONS

Most common adverse reactions (≥ 10%) in adults are: diarrhea, flatulence, and headache. (6.1)

To report SUSPECTED ADVERSE REACTIONS, contact Amgen Inc. at 1-800-77-AMGEN (1-800-772-6436) or FDA at 1-800-FDA-1088 or www.fda.gov/medwatch.

7 DRUG INTERACTIONS

- Corticosteroids, valproic acid, or haloperidol: May increase plasma ammonia level; monitor ammonia levels closely. (7.1)
- Probenecid: May affect renal excretion of metabolites of RAVICTI, including phenylacetylglutamine (PAGN) and PAA. (7.2)
- CYP3A4 Substrates with narrow therapeutic index (e.g., alfentanil, quinidine, cyclosporine): RAVICTI may decrease exposure; monitor for decreased efficacy of the narrow therapeutic index drug. (7.3)
- Midazolam: Decreased exposure; monitor for suboptimal effect of midazolam. (7.3)

8 USE IN SPECIFIC POPULATIONS

Lactation: Breastfeeding is not recommended. (8.2)

FULL PRESCRIBING INFORMATION

1 INDICATIONS AND USAGE

RAVICTI is indicated for use as a nitrogen-binding agent for chronic management of patients with urea cycle disorders (UCDs) who cannot be managed by dietary protein restriction and/or amino acid supplementation alone. RAVICTI must be used with dietary protein restriction and, in some cases, dietary supplements (e.g., essential amino acids, arginine, citrulline, protein-free calorie supplements).

Limitations of Use:

- RAVICTI is not indicated for the treatment of acute hyperammonemia in patients with UCDs because more rapidly acting interventions are essential to reduce plasma ammonia levels.
- The safety and efficacy of RAVICTI for the treatment of N-acetylglutamate synthase (NAGS) deficiency has not been established.

2 DOSAGE AND ADMINISTRATION

2.1 Important Administration Instructions

RAVICTI should be prescribed by a physician experienced in the management of UCDs.

- Instruct patients to take RAVICTI with food or formula and to administer directly into the mouth via oral syringe.
- Instruct patients to use the RAVICTI bottle and oral syringe as follows:
  - Use a new reclosable bottle cap adapter with each new bottle that is opened.
  - Open the RAVICTI bottle and twist on the new reclosable bottle cap adapter.
  - Use a new and dry oral syringe to withdraw each prescribed dose of RAVICTI.
  - Discard the oral syringe after each dose.
  - Tightly close the tethered tab on the reclosable bottle cap adapter after each use.
  - Do not rinse the reclosable bottle cap adapter.
  - Discard bottle and any remaining contents 28 days after opening.
  - If water or moisture enters the RAVICTI bottle, the contents will become cloudy in appearance. If the contents of the bottle appear cloudy at any time, do not use the remaining RAVICTI in the bottle and return it to the pharmacy to be discarded.
- Instruct that RAVICTI should be administered just prior to breastfeeding in infants who are breastfeeding.
- For patients who cannot swallow, see the instructions on administration of RAVICTI by nasogastric tube or gastrostomy tube [see Dosage and Administration (2.6)].
- For patients who require a volume of less than 1 mL per dose via nasogastric or gastrostomy tube, the delivered dose may be less than anticipated. Closely monitor these patients using ammonia levels [see Dosage and Administration (2.6)].
- The recommended dosages for patients switching from sodium phenylbutyrate to RAVICTI and patients naïve to phenylbutyric acid are different [see Dosage and Administration (2.2, 2.3)]. For both subpopulations:
  - Patients 2 years of age and older: Give RAVICTI in 3 equally divided dosages, each rounded up to the nearest 0.5 mL
  - Patients less than 2 years: Give RAVICTI in 3 or more equally divided dosages, each rounded up to the nearest 0.1 mL.
  - The maximum total daily dosage is 17.5 mL (19 g).
  - RAVICTI must be used with dietary protein restriction and, in some cases, dietary supplements (e.g., essential amino acids, arginine, citrulline, protein-free calorie supplements).

2.2 Switching From Sodium Phenylbutyrate to RAVICTI

Patients switching from sodium phenylbutyrate to RAVICTI should receive the dosage of RAVICTI that contains the same amount of phenylbutyric acid. The conversion is as follows:

Total daily dosage of RAVICTI (mL) = total daily dosage of sodium phenylbutyrate tablets (g) × 0.86

Total daily dosage of RAVICTI (mL) = total daily dosage of sodium phenylbutyrate powder (g) × 0.81

2.3 Initial Dosage in Phenylbutyrate-Naïve Patients

The recommended dosage range, based upon body surface area, in patients naïve to phenylbutyrate (PBA) is 4.5 to 11.2 mL/m^2/day (5 to 12.4 g/m^2/day). For patients with some residual enzyme activity who are not adequately controlled with protein restriction, the recommended starting dosage is 4.5 mL/m^2/day.

In determining the starting dosage of RAVICTI in treatment-naïve patients, consider the patient's residual urea synthetic capacity, dietary protein requirements, and diet adherence. Dietary protein is approximately 16% nitrogen by weight. Given that approximately 47% of dietary nitrogen is excreted as waste and approximately 70% of an administered PBA dose will be converted to urinary phenylacetylglutamine (U-PAGN), an initial estimated RAVICTI dose for a 24-hour period is 0.6 mL RAVICTI per gram of dietary protein ingested per 24-hour period. The total daily dosage should not exceed 17.5 mL.

2.4 Dosage Adjustment and Monitoring

During treatment with RAVICTI, patients should be followed clinically and with plasma ammonia levels to determine the need for dosage titration. Closely monitor plasma ammonia levels during treatment with RAVICTI and when changing the dosage of RAVICTI.

The methods used for measuring plasma ammonia levels vary among individual laboratories and values obtained using different assay methods may not be interchangeable. Normal ranges and therapeutic target levels for plasma ammonia depend upon the assay method used by the individual laboratory. During treatment with RAVICTI, refer to the assay-specific normal ranges and to the therapeutic target ranges for plasma ammonia.

Normal Plasma Ammonia

In patients treated with RAVICTI who experience neurologic symptoms (e.g., nausea, vomiting, headache, somnolence or confusion) in the absence of high plasma ammonia or other intercurrent illness to explain these symptoms, consider reducing the RAVICTI dosage and clinically monitor patients for potential neurotoxicity from high phenylacetate (PAA) concentrations. If available, obtain measurements of plasma PAA concentrations and plasma phenylacetylglutamine (PAGN) to calculate the ratio of plasma PAA to PAGN which may help to guide RAVICTI dosing. The PAA to PAGN ratio has generally been less than 1 in patients with UCDs who did not have significant plasma PAA accumulation. In general, a high PAA to PAGN ratio may indicate a slower or less efficient conjugation reaction to form PAGN, which may lead to increases in PAA without further conversion to PAGN [see Warnings and Precautions (5.1), Clinical Pharmacology (12.3)].

Elevated Plasma Ammonia

In patients 6 years and older, when plasma ammonia is elevated, increase the RAVICTI dosage to maintain fasting plasma ammonia to less than half the upper limit of normal (ULN). In infants and pediatric patients below 6 years of age, if obtaining fasting ammonia is problematic due to frequent feedings, adjust the RAVICTI dosage to keep the first ammonia of the morning below the ULN for age. If available, the ratio of PAA to PAGN in the same plasma sample may provide additional information to assist in dosage adjustment decisions [see Use in Specific Populations (8.7), Clinical Pharmacology (12.3)].

Dietary Protein Intake

If available, urinary phenylacetylglutamine (U-PAGN) measurements may be used to help guide RAVICTI dosage adjustment. Each gram of U-PAGN excreted over 24 hours covers waste nitrogen generated from 1.4 grams of dietary protein. If U-PAGN excretion is insufficient to cover daily dietary protein intake and the fasting ammonia is greater than half the ULN, the RAVICTI dosage should be increased. The amount of dosage adjustment should factor in the amount of dietary protein that has not been covered, as indicated by the 24-hour U-PAGN output, and the estimated RAVICTI dose needed per gram of dietary protein ingested and the maximum total daily dosage (i.e., 17.5 mL).

Consider a patient's use of concomitant medications, such as probenecid, when making dosage adjustment decisions based on U-PAGN. Probenecid may result in a decrease of the urinary excretion of PAGN [see Drug Interactions (7.2)].

2.5 Dosage Modifications in Patients with Hepatic Impairment

For patients with moderate to severe hepatic impairment, the recommended starting dosage is at the lower end of the recommended dosing range (4.5 mL/m^2/day) and the dosage should be kept at the lowest necessary to control the patient's plasma ammonia [see Use in Specific Populations (8.7)].

2.6 Preparation for Nasogastric Tube or Gastrostomy Tube Administration

It is recommended that all patients who can swallow take RAVICTI orally, even those with nasogastric and/or gastrostomy tubes. For patients who cannot swallow, a nasogastric tube or gastrostomy tube may be used to administer RAVICTI as follows:

- Utilize a new dry oral syringe to withdraw each prescribed dosage of RAVICTI from the bottle.
- Place the tip of the syringe into the nasogastric/gastrostomy tube.
- Utilizing the plunger of the syringe, administer RAVICTI into the tube.
- Use a separate syringe to flush the nasogastric/gastrostomy tube. Flush once with 10 mL of water or formula and allow the flush to drain.
- If needed, flush a second time with an additional 10 mL of water or formula to clear the tube.

For patients who require a volume of less than 1 mL per dose via nasogastric or gastrostomy tube, the delivered dosage may be less than anticipated due to adherence of RAVICTI to the plastic tubing. Therefore, these patients should be closely monitored using ammonia levels following initiation of RAVICTI dosing or dosage adjustments.

3 DOSAGE FORMS AND STRENGTHS

Oral liquid: colorless to pale yellow, 1.1 g/mL of glycerol phenylbutyrate (delivers 1.02 g/mL of phenylbutyrate).

4 CONTRAINDICATIONS

RAVICTI is contraindicated in patients with known hypersensitivity to phenylbutyrate. Signs of hypersensitivity include wheezing, dyspnea, coughing, hypotension, flushing, nausea, and rash.

5 WARNINGS AND PRECAUTIONS

5.1 Neurotoxicity

Increased exposure to PAA, the major metabolite of RAVICTI, may be associated with neurotoxicity in patients with UCDs. In a study of adult cancer patients, subjects received sodium phenylacetate administered as a 1-hour infusion twice daily at two dose levels of 125 and 150 mg/kg for a 2-week period. Of 18 subjects enrolled, 7 had a history of primary central nervous system tumor. Signs and symptoms of potential PAA neurotoxicity, which were reversible, were reported at plasma PAA concentrations above 500 micrograms/mL and included somnolence, fatigue, lightheadedness, headache, dysgeusia, hypoacusis, disorientation, impaired memory, and exacerbation of preexisting neuropathy. PAA concentrations were not measured when symptoms resolved.

In healthy subjects, after administration of 4 mL and 6 mL RAVICTI 3 times daily (13.2 g/day and 19.8 g/day, respectively) for 3 days, a dose-dependent increase in non-serious nervous system adverse reactions were observed. In subjects who had nervous system adverse reactions, plasma PAA concentrations, which were measured on Day 3 per protocol and not always at onset of symptoms, ranged from 8 to 56 micrograms/mL with 4 mL RAVICTI 3 times daily and from 31 to 242 micrograms/mL with 6 mL RAVICTI 3 times daily.

In clinical trials in patients with UCDs who had been on sodium phenylbutyrate prior to administration of RAVICTI, adverse reactions of headache, fatigue, symptoms of peripheral neuropathy, seizures, tremor and/or dizziness were reported. No correlation between plasma PAA concentration and neurologic symptoms was identified but plasma PAA concentrations were generally not consistently measured at the time of neurologic symptom occurrence [see Clinical Pharmacology (12.3)].

If symptoms of vomiting, nausea, headache, somnolence or confusion are present in the absence of high ammonia or other intercurrent illness which explains these symptoms, consider the potential for PAA neurotoxicity which may need reduction in the RAVICTI dosage [see Dosage and Administration (2.4)].

5.2 Pancreatic Insufficiency or Intestinal Malabsorption

Exocrine pancreatic enzymes hydrolyze RAVICTI in the small intestine, separating the active moiety, phenylbutyrate, from glycerol. This process allows phenylbutyrate to be absorbed into the circulation. Low or absent pancreatic enzymes or intestinal disease resulting in fat malabsorption may result in reduced or absent digestion of RAVICTI and/or absorption of phenylbutyrate and reduced control of plasma ammonia. Monitor ammonia levels closely in patients with pancreatic insufficiency or intestinal malabsorption.

6 ADVERSE REACTIONS

The following clinically significant adverse reactions are described elsewhere in the labeling:

- Neurotoxicity [see Warnings and Precautions (5.1)]
- Pancreatic insufficiency or Intestinal Malabsorption [see Warnings and Precautions (5.2)]

6.1 Clinical Trials Experience

Because clinical trials are conducted under widely varying conditions, adverse reaction rates observed in the clinical trials of a drug cannot be directly compared to rates in the clinical trials of another drug and may not reflect the rates observed in clinical practice.

Assessment of adverse reactions was based on exposure of 45 adult patients (31 female and 14 male) with UCD subtype deficiencies of ornithine transcarbamylase (OTC, n = 40), carbamoyl phosphate synthetase (CPS, n = 2), and argininosuccinate synthetase (ASS, n = 1) in a randomized, double-blind, active-controlled (RAVICTI vs sodium phenylbutyrate), crossover, 4-week study (Study 1) that enrolled patients 18 years of age and older [see Clinical Studies (14.1)]. One of the 45 patients received only sodium phenylbutyrate prior to withdrawing on Day 1 of the study due to an adverse reaction.

The most common adverse reactions (occurring in at least 10% of patients) reported during short-term treatment with RAVICTI were diarrhea, flatulence, and headache. Table 1 summarizes adverse reactions occurring in 2 or more patients treated with RAVICTI or sodium phenylbutyrate (incidence of at least 4% in either treatment arm).

Table 1: Adverse Reactions Reported in 2 or More Adult Patients with UCDs (at least 4% in Either Treatment Arm) in Study 1
 | Number (%) of Patients in Study 1
 | Sodium Phenylbutyrate (N = 45) | RAVICTI (N = 44)
Diarrhea | 3 (7) | 7 (16)
Headache | 4 (9) | 6 (14)
Flatulence | 1 (2) | 6 (14)
Abdominal pain | 2 (4) | 3 (7)
Vomiting | 2 (4) | 3 (7)
Decreased appetite | 2 (4) | 3 (7)
Fatigue | 1 (2) | 3 (7)
Dyspepsia | 3 (7) | 2 (5)
Nausea | 3 (7) | 1 (2)
Dizziness | 4 (9) | 0
Abdominal discomfort | 3 (7) | 0

Other Adverse Reactions

RAVICTI has been evaluated in 77 patients with UCDs (51 adult and 26 pediatric patients ages 2 years to 17 years) in 2 open-label long-term studies, in which 69 patients completed 12 months of treatment with RAVICTI (median exposure = 51 weeks). During these studies there were no deaths.

Adverse reactions reported in at least 10% of adult patients were nausea, vomiting, diarrhea, decreased appetite, dizziness, headache, and fatigue.

Adverse reactions reported in at least 10% of pediatric patients ages 2 years to 17 years were upper abdominal pain, rash, nausea, vomiting, diarrhea, decreased appetite, and headache.

RAVICTI has been evaluated in 17 patients with UCDs ages 2 months to less than 2 years in 3 open-label studies. The median exposure was 6 months (range: 0.2 to 20 months). Adverse reactions reported in at least 10% of pediatric patients aged 2 months to less than 2 years were neutropenia, vomiting, constipation, diarrhea, pyrexia, hypophagia, cough, nasal congestion, rhinorrhea, rash, and papule.

RAVICTI has been evaluated in 16 patients with UCDs less than 2 months of age (age range 0.1 to 2 months, median age 0.5 months) in a single, open-label study. The median exposure was 10 months (range: 2 to 20 months). Adverse reactions reported in at least 10% of pediatric patients aged less than 2 months were vomiting, rash, gastroesophageal reflux, increased hepatic enzymes, feeding disorder (decreased appetite, hypophagia), anemia, cough, dehydration, metabolic acidosis, thrombocytosis, thrombocytopenia, neutropenia, lymphocytosis, diarrhea, flatulence, constipation, pyrexia, lethargy, and irritability/agitation.

6.2 Postmarketing Experience

The following adverse reactions have been identified during post-approval use of RAVICTI. Because these reactions are reported voluntarily from a population of uncertain size, it is not always possible to reliably estimate their frequency or establish a causal relationship to drug exposure:

- Abnormal body odor, including from skin, hair and urine
- Retching and gagging
- Dysgeusia or burning sensation in mouth

7 DRUG INTERACTIONS

7.1 Potential for Other Drugs to Affect Ammonia

Corticosteroids

Use of corticosteroids may cause the breakdown of body protein and increase plasma ammonia levels. Monitor ammonia levels closely when corticosteroids and RAVICTI are used concomitantly.

Valproic Acid and Haloperidol

Hyperammonemia may be induced by haloperidol and by valproic acid. Monitor ammonia levels closely when use of valproic acid or haloperidol is necessary in patients with UCDs.

7.2 Potential for Other Drugs to Affect RAVICTI

Probenecid

Probenecid may inhibit the renal excretion of metabolites of RAVICTI including PAGN and PAA.

7.3 Potential for RAVICTI to Affect Other Drugs

Drugs with Narrow Therapeutic Index That are Substrates of CYP3A4

RAVICTI is a weak inducer of CYP3A4 in humans. Concomitant use of RAVICTI may decrease the systemic exposure to drugs that are substrates of CYP3A4. Monitor for decreased efficacy of drugs with narrow therapeutic index (e.g., alfentanil, quinidine, cyclosporine) [see Clinical Pharmacology (12.3)].

Midazolam

Concomitant use of RAVICTI decreased the systemic exposure of midazolam. Monitor for suboptimal effect of midazolam in patients who are being treated with RAVICTI.

8 USE IN SPECIFIC POPULATIONS

8.1 Pregnancy

Risk Summary

Limited available data with RAVICTI use in pregnant women are insufficient to inform a drug-associated risk of major birth defects and miscarriage. In an animal reproduction study, administration of oral glycerol phenylbutyrate to pregnant rabbits during organogenesis at doses up to 2.7-times the dose of 6.87 mL/m^2/day in adult patients resulted in maternal toxicity, but had no effects on embryo-fetal development. In addition, there were no adverse developmental effects with administration of oral glycerol phenylbutyrate to pregnant rats during organogenesis at 1.9 times the dose of 6.87 mL/m^2/day in adult patients; however, maternal toxicity, reduced fetal weights, and variations in skeletal development were observed in pregnant rats administered oral glycerol phenylbutyrate during organogenesis at doses greater than or equal to 5.7 times the dose of 6.87 mL/m^2/day in adult patients [see Data]. Report pregnancies to Amgen Inc. at 1-800-77-AMGEN (1-800-772-6436).

The estimated background risk of major birth defects and miscarriage for the indicated population is unknown. All pregnancies have a background risk of birth defect, loss or other adverse outcomes. In the U.S. general population, the estimated background risk of major birth defects and miscarriage in clinically recognized pregnancies is 2 to 4% and 15 to 20%, respectively.

Data

Animal Data

Oral administration of glycerol phenylbutyrate during the period of organogenesis up to 350 mg/kg/day in rabbits produced maternal toxicity, but no effects on embryo-fetal development. The dose of 350 mg/kg/day in rabbits is approximately 2.7 times the dose of 6.87 mL/m^2/day in adult patients, based on combined area under the plasma concentration-time curve [AUCs] for PBA and PAA. In rats, at an oral dose of 300 mg/kg/day of glycerol phenylbutyrate (1.9 times the dose of 6.87 mL/m^2/day in adult patients, based on combined AUCs for PBA and PAA) during the period of organogenesis, no effects on embryo-fetal development were observed. Doses of 650 mg/kg/day or greater produced maternal toxicity and adverse effects on embryo-fetal development including reduced fetal weights and cervical ribs at the 7th cervical vertebra. The dose of 650 mg/kg/day in rats is approximately 5.7 times the dose of 6.87 mL/m^2/day in adult patients, based on combined AUCs for PBA and PAA. No developmental abnormalities, effects on growth, or effects on learning and memory were observed through maturation of offspring following oral administration in pregnant rats with up to 900 mg/kg/day of glycerol phenylbutyrate (8.5 times the dose of 6.87 mL/m^2/day in adult patients, based on combined AUCs for PBA and PAA) during organogenesis and lactation.

8.2 Lactation

Risk Summary

There are no data on the presence of RAVICTI in human milk, the effects on the breastfed infant, or the effects on milk production. Because of the potential for serious adverse reactions, including neurotoxicity and tumorigenicity in a breastfed infant, advise patients that breastfeeding is not recommended during treatment with RAVICTI.

8.4 Pediatric Use

Patients 2 Years to 17 Years of Age

The safety and effectiveness of RAVICTI in patients 2 years to less than 18 years of age have been established in 3 clinical studies: 2 open-label, fixed-sequence, switchover clinical studies from sodium phenylbutyrate to RAVICTI, and 1 long-term, open-label safety study [see Adverse Reactions (6.1), Clinical Studies (14.2)].

Patients Less Than 2 Years of Age

The safety and effectiveness of RAVICTI in patients with UCDs less than 2 years of age have been established in 3 open-label studies. Pharmacokinetics and pharmacodynamics (plasma ammonia), and safety were studied in 17 patients aged 2 months to less than 2 years of age and in 16 patients less than 2 months of age [see Adverse Reactions (6.1), Clinical Studies (14.3)].

Juvenile Animal Toxicity Data

In a juvenile rat study with daily oral dosing performed on postpartum Day 2 through mating and pregnancy after maturation, terminal body weight was dose-dependently reduced by up to 16% in males and 12% in females at 900 mg/kg/day or higher (3 times the dose of 6.87 mL/m^2/day in adult patients, based on combined AUCs for PBA and PAA). Learning, memory, and motor activity endpoints were not affected. However, fertility (number of pregnant rats) was decreased by up to 25% at 650 mg/kg/day or higher (2.6 times the dose of 6.87 mL/m^2/day in adult patients, based on combined AUCs for PBA and PAA).

8.5 Geriatric Use

Clinical studies of RAVICTI did not include sufficient numbers of subjects 65 years of age and older to determine whether they respond differently than younger subjects. Other reported clinical experience has not identified differences in responses between the elderly and younger patients. In general, dose selection for an elderly patient should be cautious, usually starting at the low end of the dosing range, reflecting the greater frequency of decreased hepatic, renal, or cardiac function, and of concomitant disease or other drug therapy.

8.6 Renal Impairment

The efficacy and safety of RAVICTI in patients with renal impairment are unknown. Monitor ammonia levels closely when starting patients with impaired renal function on RAVICTI.

8.7 Hepatic Impairment

No studies were conducted in patients with UCDs and hepatic impairment. Because conversion of PAA to PAGN occurs in the liver, patients with hepatic impairment may have reduced conversion capability and higher plasma PAA and PAA to PAGN ratio [see Clinical Pharmacology (12.3)]. Therefore, dosage for patients with moderate to severe hepatic impairment should be started at the lower end of the recommended dosing range and should be kept on the lowest dose necessary to control their ammonia levels [see Dosage and Administration (2.5)].

10 OVERDOSAGE

While there is no experience with overdosage in human clinical trials, PAA, a toxic metabolite of RAVICTI, can accumulate in patients who receive an overdose [see Warnings and Precautions (5.1)].

If over-exposure occurs, call your Poison Control Center at 1-800-222-1222 for current information on the management of poisoning or overdosage.

11 DESCRIPTION

RAVICTI (glycerol phenylbutyrate) is a clear, colorless to pale yellow oral liquid. It is insoluble in water and most organic solvents, and it is soluble in dimethylsulfoxide (DMSO) and greater than 65% acetonitrile.

Glycerol phenylbutyrate is a nitrogen-binding agent. It is a triglyceride containing 3 molecules of PBA linked to a glycerol backbone, the chemical name of which is benzenebutanoic acid, 1', 1' ' –(1,2,3-propanetriyl) ester with a molecular weight of 530.67. It has a molecular formula of C33H38O6. The structural formula is:

12 CLINICAL PHARMACOLOGY

12.1 Mechanism of Action

UCDs are inherited deficiencies of enzymes or transporters necessary for the synthesis of urea from ammonia (NH3, NH4^+). Absence of these enzymes or transporters results in the accumulation of toxic levels of ammonia in the blood and brain of affected patients. RAVICTI is a triglyceride containing 3 molecules of PBA. PAA, the major metabolite of PBA, is the active moiety of RAVICTI. PAA conjugates with glutamine (which contains 2 molecules of nitrogen) via acetylation in the liver and kidneys to form PAGN, which is excreted by the kidneys (Figure 1). On a molar basis, PAGN, like urea, contains 2 moles of nitrogen and provides an alternate vehicle for waste nitrogen excretion.

Figure 1: RAVICTI Mechanism of Action

12.2 Pharmacodynamics

Pharmacological Effects

In clinical studies, total 24-hour area under the plasma concentration-time curve (AUC) of ammonia levels was comparable at steady state during the switchover period between RAVICTI and sodium phenylbutyrate [see Clinical Studies (14)].

Cardiac Electrophysiology

The effect of multiple doses of RAVICTI 13.2 g/day and 19.8 g/day (approximately 69% and 104% of the maximum recommended daily dosage) on QTc interval was evaluated in a randomized, placebo- and active-controlled (moxifloxacin 400 mg), four-treatment-arm, crossover study in 57 healthy subjects. The upper bound of the one-sided 95% CI for the largest placebo-adjusted, baseline-corrected QTc, based on individual correction method (QTcI) for RAVICTI, was below 10 ms.

12.3 Pharmacokinetics

Absorption

RAVICTI is a pro-drug of PBA. Upon oral ingestion, PBA is released from the glycerol backbone in the gastrointestinal tract by lipases. PBA derived from RAVICTI is further converted by β-oxidation to PAA.

In healthy, fasting adult subjects receiving a single oral dose of 2.9 mL/m^2 of RAVICTI, peak plasma levels of PBA, PAA, and PAGN occurred at 2 hours, 4 hours, and 4 hours, respectively. Upon single-dose administration of RAVICTI, plasma concentrations of PBA were quantifiable in 15 of 22 participants at the first sample time postdose (0.25 hours). Mean maximum concentration (Cmax) for PBA, PAA, and PAGN was 37.0 micrograms/mL, 14.9 micrograms/mL, and 30.2 micrograms/mL, respectively. In healthy subjects, intact glycerol phenylbutyrate was detected in plasma. While the study was inconclusive, the incomplete hydrolysis of glycerol phenylbutyrate cannot be ruled out.

In healthy subjects, the systemic exposure to PAA, PBA, and PAGN increased in a dose-dependent manner. Following 4 mL of RAVICTI 3 times a day for 3 days, the mean Cmax and AUC were 66 micrograms/mL and 930 micrograms∙h/mL for PBA and 28 micrograms/mL and 942 micrograms∙h/mL for PAA, respectively. In the same study, following 6 mL of RAVICTI three times a day for 3 days, mean Cmax and AUC were 100 micrograms/mL and 1400 micrograms∙h/mL for PBA and 65 µg/mL and 2064 micrograms∙h/mL for PAA, respectively.

In adult patients with UCDs receiving multiple doses of RAVICTI, maximum plasma concentrations at steady state (Cmax,ss) of PBA, PAA, and PAGN occurred at 8 hours, 12 hours, and 10 hours, respectively, after the first dose in the day. Intact glycerol phenylbutyrate was not detectable in plasma in patients with UCDs.

In clinical studies of RAVICTI in patients with UCDs, the peak observed PAA concentrations by age group are shown in Table 2.

Table 2: Peak PAA Concentrations in Patients with UCDs Treated with RAVICTI in Clinical Trials
Age Range | RAVICTI Dose | Mean Peak PAA Concentration [micrograms/mL] (SD) | Median Peak PAA Concentration (Range)
Less than 2 months (n = 16) | 3.1 to 12.7 mL/m^2/day (3.4 to 14 g/m^2/day) | 257 (162) | 205 (96 to 707)
2 months to less than 2 years (n = 17) | 3.3 to 12.3 mL/m^2/day (3.7 to 13.5 g/m^2/day) | 142 (299) | 35 (1 to 1215)
2 years to 17 years (n = 53) | 1.4 to 13.7 mL/m^2/day (1.5 to 15.1 g/m^2/day) | 70 (79) | 50 (1 to 410)
Adults (n = 43) | 0.6 to 14 mL/m^2/day (0.7 to 15.4 g/m^2/day) | 39 (40) | 25 (1.6 to 178)

Distribution

In vitro, the extent of plasma protein binding for ^14C-labeled metabolites was 81% to 98% for PBA (over 1 to 250 micrograms/mL), and 37% to 66% for PAA (over 5 to 500 micrograms/mL). The protein binding for PAGN was 7% to 12% and no concentration effects were noted.

Elimination

Metabolism

Upon oral administration, pancreatic lipases hydrolyze RAVICTI (i.e., glycerol phenylbutyrate), and release PBA. PBA undergoes β-oxidation to PAA, which is conjugated with glutamine in the liver and in the kidney through the enzyme phenylacetyl-CoA: L-glutamine-N-acetyltransferase to form PAGN. PAGN is subsequently eliminated in the urine.

Saturation of conjugation of PAA and glutamine to form PAGN was suggested by increases in the ratio of plasma PAA to PAGN with increasing dose and with increasing severity of hepatic impairment.

In healthy subjects, after administration of 4 mL, 6 mL, and 9 mL 3 times daily for 3 days, the ratio of mean AUC0-23h of PAA to PAGN was 1, 1.25, and 1.6, respectively. In a separate study, in patients with hepatic impairment (Child-Pugh B and C), the ratios of mean Cmax values for PAA to PAGN among all patients dosed with 6 mL and 9 mL twice daily were 3 and 3.7.

In in vitro studies, the specific activity of lipases for glycerol phenylbutyrate was in the following decreasing order: pancreatic triglyceride lipase, carboxyl ester lipase, and pancreatic lipase-related protein 2. Further, glycerol phenylbutyrate was hydrolyzed in vitro by esterases in human plasma. In these in vitro studies, a complete disappearance of glycerol phenylbutyrate did not produce molar equivalent PBA, suggesting the formation of mono- or bis-ester metabolites. However, the formation of mono- or bis-esters was not studied in humans.

Excretion

The mean (SD) percentage of administered PBA excreted as PAGN was approximately 69% (17) in adults and 66% (24) in pediatric patients with UCDs at steady state. PAA and PBA represented minor urinary metabolites, each accounting for less than 1% of the administered dose of PBA.

Specific Populations

Age: Pediatric Population

Population pharmacokinetic modeling and dosing simulations suggest body surface area to be the most significant covariate explaining the variability of PAA clearance. PAA clearance was 10.9 L/h, 16.4 L/h, and 24.4 L/h, respectively, for patients ages 3 to 5, 6 to 11, and 12 to 17 years with UCDs.

In pediatric patients with UCDs (n = 14) ages 2 months to less than 2 years, PAA clearance was 6.8 L/h.

In pediatric patients with UCDs (n = 16) ages less than 2 months, PAA clearance was 3.8 L/h. The mean peak ratio of PAA to PAGN in UCD patients aged birth to less than 2 months was higher (mean: 1.6; range: 0.1 to 7.1) than that of UCD patients aged 2 months to less than 2 years (mean: 0.5; range: 0.1 to 1.2).

Sex

In healthy adult subjects, a gender effect was found for all metabolites, with women generally having higher plasma concentrations of all metabolites than men at a given dose level. In healthy female subjects, mean Cmax for PAA was 51 and 120% higher than in male volunteers after administration of 4 mL and 6 mL 3 times daily for 3 days, respectively. The dose normalized mean AUC0-23h for PAA was 108% higher in females than in males.

Renal Impairment

The pharmacokinetics of RAVICTI in patients with impaired renal function, including those with end-stage renal disease (ESRD) or those on hemodialysis, have not been studied [see Use in Specific Populations (8.6)].

Hepatic Impairment

The effects of hepatic impairment on the pharmacokinetics of RAVICTI were studied in patients with mild, moderate and severe hepatic impairment of (Child-Pugh class A, B, and C, respectively) receiving 100 mg/kg of RAVICTI twice daily for 7 days.

Plasma glycerol phenylbutyrate was not measured in patients with hepatic impairment.

After multiple doses of RAVICTI in patients with hepatic impairment of Child-Pugh A, B, and C, geometric mean AUCt of PBA was 42%, 84%, and 50% higher, respectively, while geometric mean AUCt of PAA was 22%, 53%, and 94% higher, respectively, than in healthy subjects.

In patients with hepatic impairment of Child-Pugh A, B, and C, geometric mean AUCt of PAGN was 42%, 27%, and 22% lower, respectively, than that in healthy subjects.

The proportion of PBA excreted as PAGN in the urine in Child-Pugh A, B, and C was 80%, 58%, and 85%, respectively, and, in healthy volunteers, was 67%.

In another study in patients with moderate and severe hepatic impairment (Child-Pugh B and C), mean Cmax of PAA was 144 micrograms/mL (range: 14 to 358 micrograms/mL) after daily dosing of 6 mL of RAVICTI twice daily, while mean Cmax of PAA was 292 micrograms/mL (range: 57 to 655 micrograms/mL) after daily dosing of 9 mL of RAVICTI twice daily. The ratio of mean Cmax values for PAA to PAGN among all patients dosed with 6 mL and 9 mL twice daily were 3 and 3.7, respectively.

After multiple doses, a PAA concentration greater than 200 micrograms/mL was associated with a ratio of plasma PAA to PAGN concentrations higher than 2.5 [see Dosage and Administration (2.5)].

Drug Interaction Studies

In vitro PBA or PAA did not induce CYP1A2, suggesting that in vivo drug interactions via induction of CYP1A2 is unlikely.

In in vitro studies, PBA at a concentration of 800 micrograms/mL caused greater than 60% reversible inhibition of cytochrome P450 isoenzymes CYP2C9, CYP2D6, and CYP3A4/5 (testosterone 6β-hydroxylase activity). The in vitro study suggested that in vivo drug interactions with substrates of CYP2D6 cannot be ruled out. The inhibition of CYP isoenzymes 1A2, 2C8, 2C19, and 2D6 by PAA at the concentration of 2.8 mg/mL was observed in vitro. Clinical implication of these results is unknown.

Effects of RAVICTI on Other Drugs

Midazolam

In healthy subjects, when oral midazolam was administered after multiple doses of RAVICTI (4 mL three times a day for 3 days) under fed conditions, the mean Cmax and AUC for midazolam were 25% and 32% lower, respectively, compared to administration of midazolam alone. In addition, the mean Cmax and AUC for 1-hydroxy midazolam were 28% and 58% higher, respectively, compared to administration of midazolam alone [see Drug Interactions (7.3)].

Celecoxib

Concomitant administration of RAVICTI did not significantly affect the pharmacokinetics of celecoxib, a substrate of CYP2C9. When 200 mg of celecoxib was orally administered with RAVICTI after multiple doses of RAVICTI (4 mL three times a day for 6 days) under fed conditions (a standard breakfast was consumed 5 minutes after celecoxib administration), the mean Cmax and AUC for celecoxib were 13% and 8% lower than after administration of celecoxib alone.

13 NONCLINICAL TOXICOLOGY

13.1 Carcinogenesis, Mutagenesis, Impairment of Fertility

Carcinogenesis

In a 2-year study in Sprague-Dawley rats, glycerol phenylbutyrate caused a statistically significant increase in the incidence of pancreatic acinar cell adenoma, carcinoma, and combined adenoma or carcinoma at a dose of 650 mg/kg/day in males (4.7 times the dose of 6.9 mL/m^2/day in adult patients, based on combined AUCs for PBA and PAA) and 900 mg/kg/day in females (8.4 times the dose of 6.9 mL/m^2/day in adult patients, based on combined AUCs for PBA and PAA). The incidence of the following tumors was also increased in female rats at a dose of 900 mg/kg/day: thyroid follicular cell adenoma, carcinoma and combined adenoma or carcinoma, adrenal cortical combined adenoma or carcinoma, uterine endometrial stromal polyp, and combined polyp or sarcoma. The dose of 650 mg/kg/day in male rats is 3 times the dose of 7.5 mL/m^2/day in pediatric patients, based on combined AUCs for PBA and PAA. The dose of 900 mg/kg/day in female rats is 5.5 times the dose of 7.5 mL/m^2/day in pediatric patients, based on combined AUCs for PBA and PAA. In a 26-week study in transgenic (Tg.rasH2) mice, glycerol phenylbutyrate was not tumorigenic at doses up to 1000 mg/kg/day.

Mutagenesis

Glycerol phenylbutyrate was not genotoxic in the Ames test, the in vitro chromosomal aberration test in human peripheral blood lymphocytes, or the in vivo rat micronucleus test. The metabolites PBA, PAA, PAGN, and phenylacetylglycine were not genotoxic in the Ames test or in vitro chromosome aberration test in Chinese hamster ovary cells.

Impairment of Fertility

Glycerol phenylbutyrate had no effect on fertility or reproductive function in male and female rats at oral doses up to 900 mg/kg/day. At doses of 1200 mg/kg/day (approximately 7 times the dose of 6.9 mL/m^2/day in adult patients, based on combined AUCs for PBA and PAA), maternal toxicity was observed and the number of nonviable embryos was increased.

14 CLINICAL STUDIES

14.1 Clinical Studies in Adult Patients with UCDs

Active-Controlled, 4-Week, Noninferiority Study (Study 1)

A randomized, double-blind, active-controlled, crossover, noninferiority study (Study 1) compared RAVICTI to sodium phenylbutyrate by evaluating ammonia levels in patients with UCDs who had been on sodium phenylbutyrate prior to enrollment for control of their UCD. Patients were required to have a confirmed diagnosis of UCD involving deficiencies of CPS, OTC, or ASS, confirmed via enzymatic, biochemical, or genetic testing. Patients had to have no clinical evidence of hyperammonemia at enrollment and were not allowed to receive drugs known to increase ammonia levels (e.g., valproate), increase protein catabolism (e.g., corticosteroids), or significantly affect renal clearance (e.g., probenecid).

The primary endpoint was the 24-hour AUC (a measure of exposure to ammonia over 24 hours) for venous ammonia on days 14 and 28 when the drugs were expected to be at steady state. Statistical noninferiority would be established if the upper limit of the 2-sided 95% CI for the ratio of the geometric means (RAVICTI/sodium phenylbutyrate) for the endpoint was 1.25 or less.

Forty-five patients were randomized 1:1 to 1 of 2 treatment arms to receive either

- Sodium phenylbutyrate for 2 weeks → RAVICTI for 2 weeks; or
- RAVICTI for 2 weeks → sodium phenylbutyrate for 2 weeks.

Sodium phenylbutyrate or RAVICTI were administered three times daily with meals. The dose of RAVICTI was calculated to deliver the same amount of PBA as the sodium phenylbutyrate dose the patients were taking when they entered the study. Forty-four patients received at least 1 dose of RAVICTI in the study.

Patients adhered to a low-protein diet and received amino acid supplements throughout the study. After 2 weeks of dosing, by which time patients had reached steady state on each treatment, all patients had 24 hours of ammonia measurements.

Demographic characteristics of the 45 patients enrolled in Study 1 were as follows: mean age at enrollment was 33 years (range: 18 to 75 years); 69% were female; 33% had adult-onset disease; 89% had OTC deficiency; 7% had ASS deficiency; 4% had CPS deficiency.

RAVICTI was non-inferior to sodium phenylbutyrate with respect to the 24-hour AUC for ammonia. Forty-four patients were evaluated in this analysis. Mean 24-hour AUCs for ammonia during steady-state dosing were 866 micromol∙h/L and 977 micromol∙h/L with RAVICTI and sodium phenylbutyrate, respectively. The ratio of geometric means was 0.91 [95% CI 0.8, 1.04].

The mean ammonia levels over 24-hours after 2 weeks of dosing (on Day 14 and 28) in the double-blind short-term study (Study 1) are displayed in Figure 2 below. The mean and median maximum ammonia levels (Cmax) over 24 hours and 24-hour AUC for ammonia are summarized in Table 3. Ammonia values across different laboratories were normalized to a common normal range of 9 to 35 micromol/L using the following formula after standardization of the units to micromol/L:

Normalized ammonia (micromol/L) = ammonia readout in micromol/L × (35/ULN of a laboratory reference range specified for each assay)

Figure 2: Ammonia Levels in Adult Patients with UCDs in Short-Term Treatment Study 1

Table 3: Ammonia Levels in Adult Patients with UCDs in Short-Term Treatment Study 1
Timepoint | Ammonia (n = 44)
Timepoint | Mean (SD) | Median (min, max)
Daily Cmax (micromol/L)
RAVICTI | 61 (46) | 51 (12, 245)
Sodium phenylbutyrate | 71 (67) | 46 (14, 303)
24-Hour AUC (micromol∙h/L)
RAVICTI | 866 (661) | 673 (206, 3351)
Sodium phenylbutyrate | 977 (865) | 653 (302, 4666)

Open-Label, Uncontrolled, Extension Study in Adults

A long-term (12-month), uncontrolled, open-label study (Study 2) was conducted to assess monthly ammonia control and hyperammonemic crisis over a 12-month period. A total of 51 adults were in the study and all but 6 had been converted from sodium phenylbutyrate to RAVICTI. Venous ammonia levels were monitored monthly. Mean fasting ammonia values in adults in Study 2 were within normal limits during long-term treatment with RAVICTI (range: 6 to 30 micromol/L). Of 51 adult patients participating in the 12-month, open-label treatment with RAVICTI, 7 patients (14%) reported a total of 10 hyperammonemic crises. The fasting ammonia measured during Study 2 is displayed in Figure 3. Ammonia values across different laboratories were normalized to a common normal range of 9 to 35 micromol/L.

Figure 3: Ammonia Levels in Adult Patients with UCDs in Long-Term Treatment Study 2

Open-Label, Long-Term Study in Adults

An open-label long-term, study (Study 5) was conducted to assess ammonia control in adult patients with UCDs. The study enrolled patients with UCDs who had completed the safety extensions of Study 1, Study 3 or Study 4 (Study 2, 3E and 4E, respectively). A total of 43 adult patients between the ages of 19 and 61 years were in the study. The median length of study participation was 1.9 years (range: 0 to 4.5 years). Venous ammonia levels were monitored at a minimum of every 6 months. Mean fasting ammonia values in adult patients in Study 5 were within normal limits during long-term (24 months) treatment with RAVICTI (range: 24.2 to 31.4 micromol/L). Of the 43 adult patients participating in the open-label treatment with RAVICTI, 9 patients (21%) reported a total of 21 hyperammonemic crises. Ammonia values across different laboratories were normalized to a common normal range of 10 to 35 micromol/L.

14.2 Clinical Studies in Pediatric Patients 2 Years to 17 Years of Age with UCDs

The efficacy of RAVICTI in pediatric patients 2 years to 17 years of age with UCDs was evaluated in 2 fixed-sequence, open-label, sodium phenylbutyrate to RAVICTI switchover studies (Studies 3 and 4). Study 3 was 7 days in duration and Study 4 was 10 days in duration.

These studies compared ammonia levels of patients on RAVICTI to ammonia levels of patients on sodium phenylbutyrate in 26 pediatric patients between 2 months and 17 years of age with UCDs. Four patients less than 2 years of age were excluded from this analysis due to insufficient data. The dose of RAVICTI was calculated to deliver the same amount of PBA as the dose of sodium phenylbutyrate that patients were taking when they entered the trial. Sodium phenylbutyrate or RAVICTI were administered in divided doses with meals. Patients adhered to a low-protein diet throughout the study. After a dosing period with each treatment, all patients underwent 24 hours of venous ammonia measurements, as well as blood and urine pharmacokinetic assessments.

UCD subtypes included OTC (n = 12), ASL (n = 8), and ASS deficiency (n = 2), and patients received a mean RAVICTI dose of 8 mL/m^2/day (8.8 g/m^2/day), with doses ranging from 1.4 to 13.1 mL/m^2/day (1.5 to 14.4 g/m^2/day). Doses in these patients were based on previous dosing of sodium phenylbutyrate.

The 24-hour AUCs for ammonia (AUC0-24h) in 11 pediatric patients 6 years to 17 years of age with UCDs (Study 3) and 11 pediatric patients 2 years to 5 years of age with UCDs (Study 4) were similar between treatments. In pediatric patients 6 years to 17 years of age, the ammonia AUC0-24h was 604 micromol∙h/L vs 815 micromol∙h/L on RAVICTI vs sodium phenylbutyrate, respectively. In patients between 2 years and 5 years of age with UCDs, the ammonia AUC0-24h was 632 micromol∙h/L vs 720 micromol∙h/L on RAVICTI versus sodium phenylbutyrate, respectively.

The mean ammonia levels over 24 hours in open-label, short-term Studies 3 and 4 at common time points are displayed in Figure 4. Ammonia values across different laboratories were normalized to a common normal range of 9 to 35 micromol/L using the following formula after standardization of the units to micromol/L:

Normalized ammonia (micromol/L) = ammonia readout in micromol/L × (35/ULN of a laboratory reference range specified for each assay)

Figure 4: Ammonia Levels in Pediatric Patients 2 Years to 17 Years of Age with UCDs in Short-Term Treatment Studies 3 and 4

Open-Label, Uncontrolled, Extension Studies in Pediatric Patients 2 Years to 17 Years of Age

Long-term (12-month), uncontrolled, open-label studies were conducted to assess monthly ammonia control and hyperammonemic crises over a 12-month period. In two studies (Study 2, which also enrolled adults, and an extension of Study 3, referred to here as Study 3E), a total of 26 pediatric patients ages 6 years to 17 years were enrolled and all but 1 had been converted from sodium phenylbutyrate to RAVICTI. Mean fasting venous ammonia levels were within normal limits (range: 17 to 23 micromol/L) during long-term treatment with RAVICTI. Of the 26 pediatric patients 6 years to 17 years of age participating in these two trials, 5 patients (19%) reported a total of 5 hyperammonemic crises. The fasting ammonia levels measured during these two extension studies in patients 6 years to 17 years are displayed in Figure 5. Ammonia values across different laboratories were normalized to a common normal range of 9 to 35 micromol/L.

Figure 5: Ammonia Levels in Pediatric Patients 2 Years to 17 Years of Age with UCDs in Long-Term Treatment Studies 2 and 3E

In an extension of Study 4 (referred to as Study 4E), after a median time on study of 4.5 months (range: 1 to 5.7 months), 2 of 16 pediatric patients ages 2 years to 5 years had experienced three hyperammonemic crises.

Open-Label, Long-Term Study in Pediatric Patients 1-Year to 17 Years of Age

An open-label, long-term study (Study 5) was conducted to assess ammonia levels in pediatric patients with UCD. The study enrolled patients with UCDs who had completed Studies 2, 3E and 4E. A total of 45 pediatric patients ages 1-year to 17 years were included in the study. The median length of treatment was 1.7 years (range: 0.2 to 4.6 years). Venous ammonia levels were monitored at a minimum every 6 months. Mean ammonia values in pediatric patients in Study 5 were within normal limits during long-term (24 months) treatment with RAVICTI (range: 15.4 to 25.1 micromol/L). Of the 45 pediatric patients participating in the open-label treatment with RAVICTI, 11 patients (24%) reported a total of 22 hyperammonemic crises. Ammonia values across different laboratories were normalized to a common normal range of 10 to 35 micromol/L.

14.3 Clinical Studies in Pediatric Patients Less Than 2 Years of Age with UCDs

The efficacy of RAVICTI in pediatric patients less than 2 years of age with UCDs was evaluated in uncontrolled, open-label studies (Studies 4/4E, 5 [see Clinical Studies (14.2)] and 6). A total of 17 pediatric patients with UCDs aged 2 months to less than 2 years participated in Studies 4/4E, 5 and 6. Study 6 enrolled 16 pediatric patients less than 2 months of age.

Uncontrolled, Open-Label Studies in Pediatric Patients Aged 2 Months to Less than 2 Years of Age (Studies 4/4E, 5)

A total of 7 patients with UCDs aged 2 months to less than 2 years participated in Studies 4/4E and 5. In these studies, there were 7, 6, 6, 6 and 3 pediatric patients who completed 1, 6, 9, 12 and 18 months, respectively (mean and median exposure of 15 and 17 months, respectively). Patients were converted from sodium phenylbutyrate to RAVICTI. The dosage of RAVICTI was calculated to deliver the same amount of PBA as the sodium phenylbutyrate dosage the patients were taking when they entered the study.

Patients received a mean RAVICTI dose of 7.5 mL/m^2/day (8.2 g/m^2/day), with doses ranging from 3.3 to 12.3 mL/m^2/day (3.7 to 13.5 g/m^2/day). Patients were dosed three times per day (n = 3) or four times per day (n = 4).

Venous ammonia levels were monitored on Days 1, 3, and 10 in Study 4 and at week 1 in Study 4E. Two patients had elevated ammonia values on Day 1 of treatment (122 micromol/L and 111 micromol/L, respectively) and neither had associated signs and symptoms of hyperammonemia. At Day 10/week 1, six of the 7 patients had normal ammonia levels (less than 100 micromol/L) while the remaining patient had an elevated ammonia value on Day 10 (168 micromol/L) and was asymptomatic.

During the extension period, venous ammonia levels were monitored monthly. Ammonia values across different laboratories were normalized (transformed) to a common normal pediatric range of 28 to 57 micromol/L for comparability. The mean ammonia levels in pediatric patients at month 1, 3, 6, 9 and 12 were 58, 49, 34, 65, and 31 micromol/L during treatment with RAVICTI, respectively.

Three patients reported a total of 3 hyperammonemic crises defined as having signs and symptoms consistent with hyperammonemia (such as frequent vomiting, nausea, headache, lethargy, irritability, combativeness, and/or somnolence) associated with high ammonia levels (greater than 100 micromol/L) and requiring medical intervention. Hyperammonemic crises were precipitated by gastroenteritis, vomiting, infection or no precipitating event (one patient). There were 4 patients who had one ammonia level that exceeded 100 micromol/L which was not associated with a hyperammonemic crisis.

Uncontrolled, Open-Label Study in Pediatric Patients Less Than 2 Years of Age (Study 6)

Study 6 was an uncontrolled, open-label study in pediatric patients less than 2 years of age. The primary efficacy endpoint was successful transition to RAVICTI within a period of 4 days followed by 3 days of observation for a total of 7 days, where successful transition was defined as no signs and symptoms of hyperammonemia and a venous ammonia level less than 100 micromol/L. Ammonia levels were monitored for up to 4 days during transition and on Day 7.

Pediatric Patients 2 Months to Less than 2 Years of Age

A total of 10 pediatric patients with UCDs aged 2 months to less than 2 years participated in Study 6, of which 6 patients converted from sodium phenylbutyrate to RAVICTI and 1 patient converted from sodium phenyl butyrate and sodium benzoate. The dosage of RAVICTI was calculated to deliver the same amount of PBA as the sodium phenylbutyrate dosage the patients were taking when they entered the trial. Two patients were treatment-naïve and received RAVICTI dosage of 7.5 mL/m^2/day and 9.4 mL/m^2/day, respectively. One additional patient was gradually discontinued from intravenous sodium benzoate and sodium phenylacetate while RAVICTI was initiated. The dosage of RAVICTI after transition was 8.5 mL/m^2/day.

There were 9, 7, 7, 4, 1 and 4 pediatric patients who completed 1, 3, 6, 12, 18 and 24 months, respectively (mean and median exposure of 9 and 9 months, respectively).

Patients received a mean RAVICTI dose of 8 mL/m^2/day (8.8 g/m^2/day), with doses ranging from 4.8 to 11.5 mL/m^2/day (5.3 to 12.6 g/m^2/day). Patients were dosed three times a day (n = 6), four times a day (n = 2), or five or more times a day (n = 2).

Nine patients successfully transitioned as defined by the primary endpoint. One additional patient developed hyperammonemia on Day 3 of dosing and experienced surgical complications (bowel perforation and peritonitis) following jejunal tube placement on Day 4. This patient developed hyperammonemic crisis on Day 6, and subsequently died of sepsis from peritonitis unrelated to drug. Although two patients had Day 7 ammonia values of 150 micromol/L and 111 micromol/L respectively, neither had associated signs and symptoms of hyperammonemia.

During the extension phase, venous ammonia levels were monitored monthly. Ammonia values across different laboratories were normalized (transformed) to a common normal pediatric range of 28 to 57 micromol/L for comparability. The mean normalized ammonia levels in pediatric patients at months 1, 2, 3, 4, 5, 6, 9, 12, 15, 18 and 24 were 67, 53, 78, 93, 78, 67, 38, 38, 36, 48 and 53 micromol/L during treatment with RAVICTI, respectively. Three patients reported a total of 7 hyperammonemic crises as defined in Study 4/4E and 5. Hyperammonemic crises were precipitated by vomiting, upper respiratory tract infection, gastroenteritis, decreased caloric intake or had no identified precipitating event (3 events). There was one additional patient who had one ammonia level that exceeded 100 micromol/L which was not associated with a hyperammonemic crisis.

Pediatric Patients Less than 2 Months of Age

A total of 16 pediatric patients less than 2 months of age participated in Study 6. Median age at enrollment was 0.5 months (range: 0.1 to 2 months). Eight patients had OTC deficiency, 7 patients had ASS deficiency, and 1 patient had ASL deficiency. Ten of the 16 patients transitioned from sodium phenylbutyrate to RAVICTI within 3 days of treatment and their initial dosage of RAVICTI was calculated to deliver the same amount of phenylbutyrate as the sodium phenylbutyrate dosage administered prior to RAVICTI dosing. Three of the 16 patients were treatment-naïve and started RAVICTI at dosages of 9, 9.4, and 9.6 mL/m^2/day. The remaining 3 of the 16 patients transitioned from intravenous sodium benzoate and sodium phenylacetate to RAVICTI within 3 days of treatment and their initial dosages of RAVICTI were 10.4, 10.9, and 10.9 mL/m^2/day.

Of the 16 patients, 16, 14, 12, 6, and 3 patients were treated for 1, 3, 6, 12, and 18 months, respectively.

After the initial 7-day transition period, patients received a mean RAVICTI dosage of 8 mL/m^2/day (8.8 g/m^2/day), with doses ranging from 3.1 to 12.7 mL/m^2/day (3.4 to 14 g/m^2/day). The frequency of dosing varied throughout the study. The majority of patients were dosed three times per day with feeding. No patients discontinued during the 7-day transition phase. Ammonia values across different laboratories were normalized (transformed) to a common normal pediatric range of 28 to 57 micromol/L for comparability.

During the safety extension phase (months 1-24), venous ammonia levels were monitored monthly for the first 6 months of treatment and every 3 months thereafter until the patients terminated or completed the study. During the safety extension phase, 1 patient discontinued from the study due to an adverse event (increased hepatic enzymes), 2 patients were withdrawn from the study by their parent/guardian, and 4 patients discontinued from the study early to undergo a liver transplant (protocol-defined discontinuation criterion). The normalized ammonia levels in pediatric patients with available values (which varied by month of treatment) in Study 6 in patients less than 2 months of age are shown in Table 4.

Table 4: Ammonia [normalized ammonia (micromol/L) = ammonia readout in micromol/L × (35/ULN of a laboratory reference range specified for each assay)] Levels in Pediatric Patients Less than 2 Months of Age with UCDs in Study 6
Month | N (patients with available ammonia level) | Normalized Ammonia (micromol/L) [normal range: 28 to 57 micromol/L.]
Month | N (patients with available ammonia level) | Mean (SD) | Median (Min, Max)
1 | 15 | 71 (52) | 60 (18, 227)
2 | 11 | 58 (40) | 50 (16, 168)
3 | 14 | 53 (34) | 46 (11, 122)
4 | 11 | 94 (106) | 64 (35, 407)
5 | 10 | 52 (18) | 57 (27, 86)
6 | 9 | 49 (24) | 42 (22, 91)
9 | 8 | 56 (34) | 45 (22, 122)
12 | 6 | 35 (17) | 36 (11, 60)
15 | 4 | 52 (12) | 52 (39, 67)
18 | 3 | 64 (14) | 63 (50, 78)
24 | 9 | 63 (29) | 72 (23, 106)

Five patients (all less than 1 month of age) experienced a total of 7 hyperammonemic crises defined as in Study 4/4E and 5. Hyperammonemic crises were precipitated by upper respiratory tract infection (2 events), change in diet (1 event), or had no identified precipitating event (4 events).

16 HOW SUPPLIED/STORAGE AND HANDLING

RAVICTI® (glycerol phenylbutyrate) oral liquid 1.1 g/mL is supplied in multi-use, 25-mL glass bottles. The bottles are supplied in the following configurations:

- NDC 75987-050-06: Single 25-mL bottle per carton
- NDC 75987-050-07: Four 25-mL bottles per carton

STORAGE AND HANDLING

Store at 20°-25°C (68°-77°F) with excursions permitted to 15°-30°C (59°-86°F). Discard bottle 28 days after opening.

17 PATIENT COUNSELING INFORMATION

Advise the patient to read the FDA-approved patient labeling (Medication Guide).

Neurotoxicity [see Warnings and Precautions (5.1)]

- Inform patients/caregivers that adverse reactions of RAVICTI are sometimes the same as symptoms of high blood ammonia. Neurological adverse reactions may also be associated with the major metabolite of RAVICTI, PAA, and may be reversible. Blood tests for PAA may be done to measure the amount of PAA in the blood. Instruct the patient/caregiver to contact the healthcare provider immediately if the patient experiences: nausea, vomiting, headache, fatigue, somnolence, lightheadedness, confusion, exacerbation of preexisting neuropathy, disorientation, impaired memory, dysgeusia, or hypoacusis.

Pregnancy

Report pregnancies to Amgen Inc. at 1-800-77-AMGEN (1-800-772-6436) [see Use in Specific Populations (8.1)].

Lactation

Advise patients that breastfeeding is not recommended during treatment with RAVICTI [see Use in Specific Populations (8.2)].

Administration

- Instruct patients to take RAVICTI with food or formula and to administer directly into the mouth via oral syringe.
- Instruct patients to use the RAVICTI bottle and oral syringe as follows:
  - Use a new reclosable bottle cap adapter with each new bottle that is opened.
  - Open the RAVICTI bottle and twist on the new reclosable bottle cap adapter.
  - Use a new and dry oral syringe to withdraw each prescribed dose of RAVICTI.
  - Discard the oral syringe after each dose.
  - Tightly close the tethered tab on the reclosable bottle cap adapter after each use.
  - Do not rinse the reclosable bottle cap adapter.
  - Discard bottle and any remaining contents 28 days after opening.
  - If water or moisture enters the RAVICTI bottle, the contents will become cloudy in appearance. If the contents of the bottle appear cloudy at any time, do not use the remaining RAVICTI in the bottle and return it to the pharmacy to be discarded.
- Instruct that RAVICTI should be administered just prior to breastfeeding in infants who are breastfeeding.
- Instruct patients to take RAVICTI orally, even if they have a nasogastric and/or gastrostomy tube. For patients who cannot swallow and who have a nasogastric tube or gastrostomy tube in place, instruct patients/caregivers to administer RAVICTI as follows:
  - Utilize a new dry oral syringe to withdraw the prescribed dosage of RAVICTI from the bottle.
  - Place the tip of the syringe into the gastrostomy/nasogastric tube.
  - Utilizing the plunger of the syringe, administer RAVICTI into the tube.
  - Use a separate syringe to flush the nasogastric/gastrostomy tube. Flush once with 10 mL of water or formula and allow the flush to drain.
  - If needed, flush a second time with an additional 10 mL of water or formula to clear the tube.

RAVICTI® (glycerol phenylbutyrate)

Manufactured for:
Horizon Therapeutics US Holdings, LLC
1 Horizon Way
Deerfield, IL 60015

© 2025 Amgen Inc. All rights reserved

1XXXXXX-V4

MEDICATION GUIDE
RAVICTI (rah-VIK- tee)
(glycerol phenylbutyrate)
oral liquid

What is the most important information I should know about RAVICTI?
RAVICTI may cause serious side effects, including:
Nervous system problems (Neurotoxicity). Phenylacetate (PAA), a breakdown product of RAVICTI, may cause nervous system side effects. Call your doctor or get medical help right away if you get any of these symptoms while taking RAVICTI:

- sleepiness
- lightheadedness
- change in taste
- problems with hearing
- confusion
- problems with memory

- worsening of numbness, tingling, or burning in your hands or feet
- headache
- feeling very tired (fatigue)
- nausea
- vomiting

Your doctor may do blood tests to measure the amount of PAA in your blood during your treatment with RAVICTI.

What is RAVICTI?

- RAVICTI is a prescription medicine used for long-term management of high blood levels of ammonia (hyperammonemia) caused by a condition called a urea cycle disorder (UCD). RAVICTI should be used if the UCD cannot be managed with a low protein diet and dietary supplements alone. RAVICTI must be used along with a low protein diet and in some cases dietary supplements.
- RAVICTI is not used for the acute treatment of hyperammonemia in people with UCD.
- It is not known if RAVICTI is safe and effective for the treatment of N-acetylglutamate synthase (NAGS) deficiency.

Do not take RAVICTI if you are allergic to phenylbutyrate. Call your doctor or go to the nearest hospital emergency room if you have wheezing, shortness of breath, cough, low blood pressure, flushing, nausea or a rash while taking RAVICTI.

Before taking RAVICTI, tell your doctor about all of your medical conditions, including if you:

- have liver or kidney problems
- have pancreas or bowel (intestine) problems
- are pregnant or plan to become pregnant. It is not known if RAVICTI will harm your unborn baby. If you become pregnant during treatment with RAVICTI, call Amgen Inc. at 1-800-77-AMGEN (1-800-772-6436). to report the pregnancy.
- are breastfeeding or plan to breastfeed. It is not known if RAVICTI passes into your breast milk. Breastfeeding is not recommended during treatment with RAVICTI. Talk to your doctor about the best way to feed your baby if you take RAVICTI.

Tell your doctor about all the medicines you take, including prescription and over-the-counter medicines, vitamins, dietary and herbal supplements.
Know the medicines you take. Keep a list of them to show your doctor and pharmacist when you get a new medicine.

How should I take RAVICTI?

- Take RAVICTI exactly as your doctor tells you.
- Your doctor will tell you how much RAVICTI to take and when to take it.
- Your doctor may change your dose if needed.
- Take RAVICTI with food or formula.
- In an infant who is breastfeeding, give RAVICTI just before breastfeeding.
- RAVICTI is an oral liquid that is taken by mouth using an oral syringe.
- Ask your pharmacist for oral syringes and a reclosable bottle cap adapter for each bottle you receive if you do not have them.
- Use the RAVICTI bottle and oral syringe as follows:
  - Use a new reclosable bottle cap adapter with each new RAVICTI bottle that is opened.
  - Open the RAVICTI bottle and twist on the new reclosable bottle cap adapter.
  - Use a new dry oral syringe to remove each prescribed dose of RAVICTI.
  - Throw away (discard) the oral syringe after each dose.
  - Tightly close the tethered tab on the reclosable bottle cap adapter after each use.
  - Do not rinse the reclosable bottle cap adapter.
  - If water or moisture enters the RAVICTI bottle, the contents will become cloudy in appearance. If the contents appear cloudy at any time, do not use the remaining RAVICTI and return the bottle to your pharmacy to throw it away.
  - Throw away the bottle and any unused RAVICTI 28 days after opening.
- If you have a nasogastric or gastrostomy tube in place and can swallow, you should take RAVICTI by mouth.
- Stay on the diet that your doctor gives you.
- If you take too much RAVICTI, call your doctor or your poison control center at 1-800-222-1222 or go to the nearest hospital emergency room right away.

For people who cannot swallow and who have a nasogastric or gastrostomy tube in place, RAVICTI should be given as follows:

- Use a new dry oral syringe to withdraw each prescribed dose of RAVICTI from the bottle.
- Place the tip of the syringe into the nasogastric or gastrostomy tube and push the plunger of the syringe to give RAVICTI into the tube.
- Use a separate syringe to flush the nasogastric or gastrostomy tube. Add 10 mL of water or formula to the syringe and push the plunger of the syringe to flush any remaining medicine from the nasogastric or gastrostomy tube into the stomach.
- If needed, flush the nasogastric or gastrostomy tube again with 10 mL of water or formula to clear the nasogastric or gastrostomy tube.

What are the possible side effects of RAVICTI?
RAVICTI may cause serious side effects, including:

- See "What is the most important information I should know about RAVICTI?"

The most common side effects of RAVICTI in adults include:

- diarrhea
- gas
- headache
- abdomen (stomach) pain

- vomiting
- tiredness
- decreased appetite
- indigestion or heartburn

The most common side effects of RAVICTI in children 2 years to 17 years of age include:

- upper abdomen (stomach) pain
- rash
- nausea
- vomiting

- diarrhea
- decreased appetite
- headache

The most common side effects of RAVICTI in children 2 months to less than 2 years of age include:

- low white blood cell count (neutropenia)
- vomiting
- constipation
- diarrhea
- fever
- reduced food intake

- cough
- stuffy nose
- runny nose
- skin rash
- small round bumps on the skin

The most common side effects of RAVICTI in children less than 2 months of age include:

- vomiting
- rash
- gastroesophageal reflux
- increased levels of liver enzymes in the blood
- decreased appetite and reduced food intake
- low red blood cell count (anemia)
- cough
- loss of too much body fluid (dehydration)
- too much acid in the blood (acidosis)
- high blood platelet count (thrombocytosis)
- low blood platelet count (thrombocytopenia)

- low blood neutrophil count (type of white blood cell) (neutropenia)
- high blood white blood cell count (lymphocytosis)
- diarrhea
- gas
- constipation
- fever
- drowsiness (lethargy)
- irritability
- agitation

These are not all of the possible side effects of RAVICTI. Call your doctor for medical advice about side effects. You may report side effects to FDA at 1-800-FDA-1088.
You may also report side effects to Amgen Inc. at 1-800-77-AMGEN (1-800-772-6436).

How should I store RAVICTI?

- Store RAVICTI between 68°F to 77°F (20°C to 25°C).

Keep RAVICTI and all medicines out of the reach of children.

General information about the safe and effective use of RAVICTI.
Medicines are sometimes prescribed for purposes other than those listed in a Medication Guide. Do not use RAVICTI for a condition for which it was not prescribed. Do not give RAVICTI to other people, even if they have the same symptoms you have. It may harm them.
You can ask your doctor or pharmacist for information about RAVICTI that is written for health professionals.

What are the ingredients in RAVICTI?
Active ingredient: glycerol phenylbutyrate
Manufactured for: Horizon Therapeutics US Holdings, LLC, 1 Horizon Way, Deerfield, IL 60015.
For more information, go to www.RAVICTI.com or call 1-800-77-AMGEN (1-800-772-6436)..

This Medication Guide has been approved by the U.S. Food and Drug Administration.

Revised: September 2025

PRINCIPAL DISPLAY PANEL - 25 mL Bottle Carton

NDC 75987-050-06

RAVICTI®
(glycerol phenylbutyrate) Oral Liquid

1.1 grams per mL

For Oral Use Only
25 mL

Pharmacist:
Dispense the enclosed
Medication Guide to patient
and/or caregiver.

AMGEN